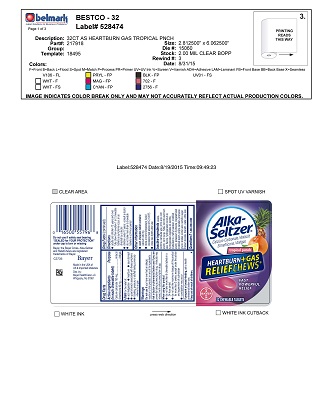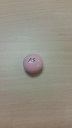 DRUG LABEL: Tropical Panned
NDC: 52642-225 | Form: TABLET, CHEWABLE
Manufacturer: BestCo Inc.
Category: otc | Type: HUMAN OTC DRUG LABEL
Date: 20160211

ACTIVE INGREDIENTS: CALCIUM CARBONATE 750 mg/1 1; DIMETHICONE 80 mg/1 1
INACTIVE INGREDIENTS: CARNAUBA WAX

Calcium carbonate 750mg
Simethicone 80mg

ACTIVE INGREDIENT

Calcium carbonate 750 mg

Simethicone 80 mg

Purpose

Antacid

Anti-gas

INDICATIONS AND USAGE

Uses for the relief of:

- Acid indigestion
- Heartburn
- Sour stomach
- Upset stomach associated with these symptoms
- Bloating, pressure, or stuffed feeling commonl referred to as gas

Warnings

Do not use if you've ever had an allergic reaction to this product or any of its ingredients

Ask a doctor or pharmacist before use if you are presently taking a prescription drug. Antacids may interact with certain prescription drugs.

When using this product

- Do not take more than 5 chewable tablets in a 24 hour period
- Do not use the maximum dosage of this product for more than 2 weeks, except under the advice and supervsion of a physician.
- Constipation may occur.

PREGNANCY OR BREAST FEEDING

If pregnant or breast-feeding, ask a health professional before use.

Keep out of reach of children

Directions

- Adutls and children 12 years and older: Fully chew then swallow 1 or 2 chewable tablets are symptoms occur, or as directed by a doctor.
- Children under 12 years: consult a doctor.
- Do not take more than 5 chewable tablets in a 24 hour period.

Other information

- each chewable tablet contains: calcium 330 mg
- store at room temperature. Avoid excessive heat above 40C (104F)
- Close cap tightly after use

Inactive ingredients

acacia, carmine, carnauba wax, citric acid, corn starch, corn syrup, FD&C Red #40 Aluminum Lake, flavors, hydrogenated coconut oil, hydrogenated vegetable oil, lecithin, maltodextrin, methyl paraben, modified starch, potassium hydroxide, pregelatinized modified starch, propyl paraben, propylene glycol, shellac, sorbic acid, sorbitol, sugar, titanium dioxide, triacetin, water, white wax

Questions

1-800-986-0369